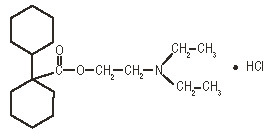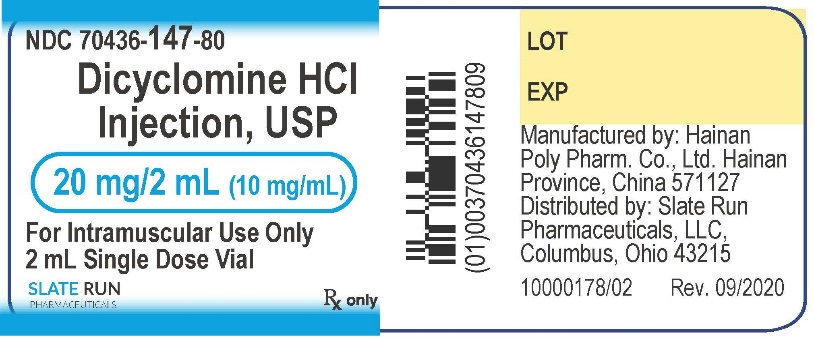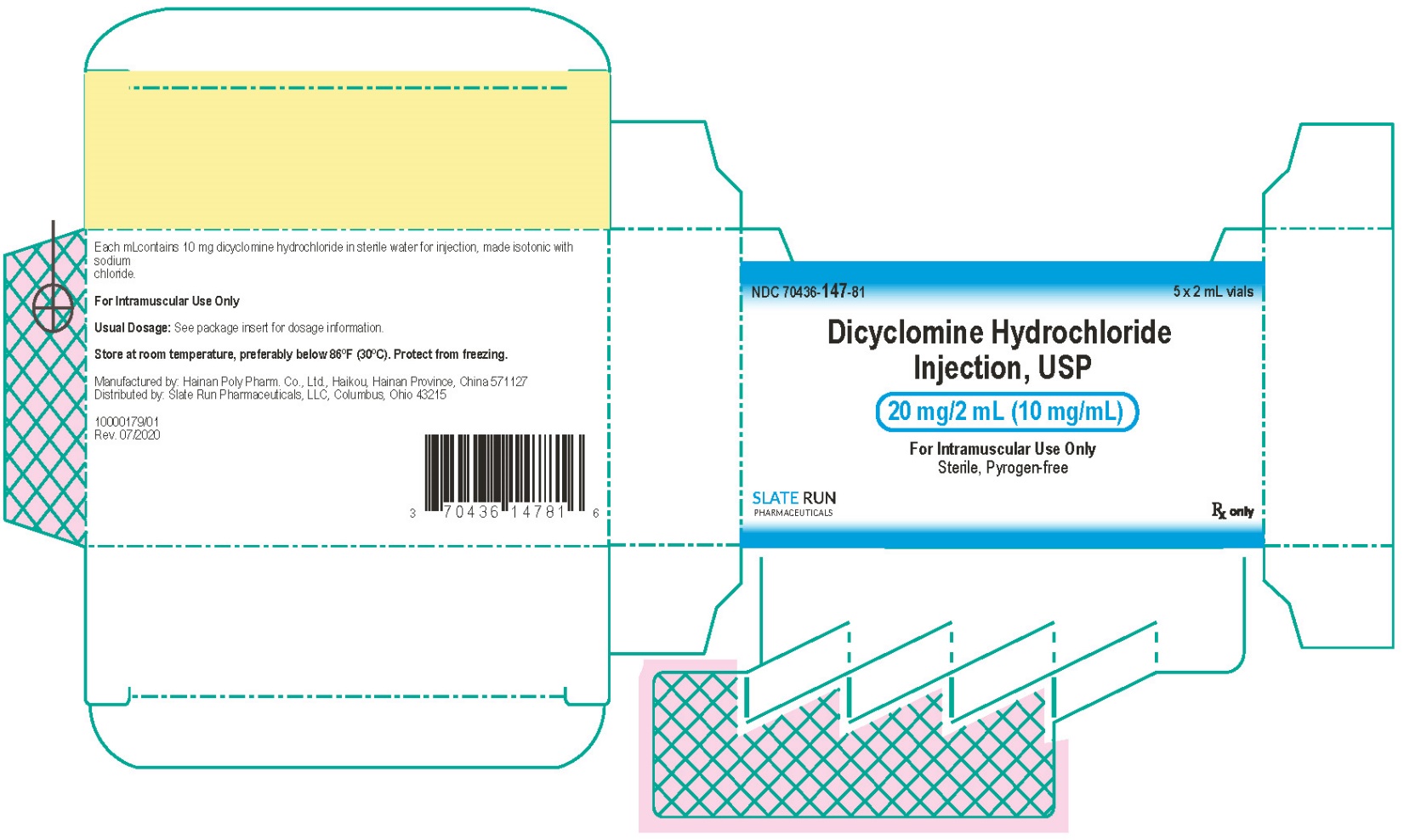 DRUG LABEL: Dicyclomine Hydrochloride
NDC: 70436-147 | Form: INJECTION
Manufacturer: Slate Run Pharmaceuticals, LLC
Category: prescription | Type: HUMAN PRESCRIPTION DRUG LABEL
Date: 20260228

ACTIVE INGREDIENTS: DICYCLOMINE HYDROCHLORIDE 20 mg/2 mL
INACTIVE INGREDIENTS: SODIUM CHLORIDE; WATER

HIGHLIGHTS OF PRESCRIBING INFORMATION

These highlights do not include all the information needed to use DICYCLOMINE HYDROCHLORIDE INJECTION safely and effectively. See full prescribing information for DICYCLOMINE HYDROCHLORIDE INJECTION.
DICYCLOMINE HYDROCHLORIDE injection, USP for intramuscular use
Initial U.S. Approval: 1950

1 INDICATIONS AND USAGE

Dicyclomine Hydrochloride is an antispasmodic and anticholinergic (antimuscarinic) agent indicated for the treatment of functional bowel/irritable bowel syndrome (1)

2 DOSAGE AND ADMINISTRATION

Dosage for dicyclomine hydrochloride must be adjusted to individual patient needs (2).

If a dose is missed, patients should continue the normal dosing schedule (2).

Intramuscular in adults (2.2):

- Intramuscular administration recommended no longer than 1 or 2 days when patients cannot take oral administration
- Recommended dose: 10 mg to 20 mg four times a day

3 DOSAGE FORMS AND STRENGTHS

- Dicyclomine Hydrochloride Injection, USP 20 mg/2 mL (10 mg/mL) (3)

4 CONTRAINDICATIONS

- Infants less than 6 months of age (4)
- Nursing mothers (4)
- Unstable cardiovascular status in acute hemorrhage (4)
- Myasthenia gravis (4)
- Glaucoma (4)
- Obstructive uropathy (4)
- Obstructive disease of the gastrointestinal tract (4)
- Severe ulcerative colitis (4)
- Reflux esophagitis (4)

5 WARNINGS AND PRECAUTIONS

- For intramuscular injection only; should not be administered by any other route. Intravenous injection may result in thrombosis or thrombophlebitis and injection site reactions (5.1)
- Cardiovascular conditions:worsening of conditions (5.2)
- Peripheral and central nervous system:heat prostration can occur with drug use (fever and heat stroke due to decreased sweating); drug should be discontinued and supportive measures instituted (5.3)
- Psychosis and delirium have been reported in patients sensitive to anticholinergic drugs (such as elderly patients and/or in patients with mental illness):signs and symptoms resolve within 12 to 24 hours after discontinuation of dicyclomine hydrochloride (5.3)
- Myasthenia Gravis:overdose may lead to muscular weakness and paralysis. Dicyclomine hydrochloride should be given to patients with myasthenia gravis only to reduce adverse muscarinic effects of an anticholinesterase (5.4)
- Incomplete intestinal obstruction:diarrhea may be an early symptom especially in patients with ileostomy or colostomy. Treatment with dicyclomine hydrochloride would be inappropriate and possibly fatal (5.5)
- Salmonella dysenteric patients: due to risk of toxic megacolon (5.6)
- Ulcerative colitis: Dicyclomine hydrochloride should be used with caution in these patients; large doses may suppress intestinal motility or aggravate the serious complications of toxic megacolon (5.7)
- Prostatic hypertrophy: Dicyclomine hydrochloride should be used with caution in these patients; may lead to urinary retention (5.8)
- Hepatic and renal disease:should be used with caution (5.9)
- Geriatric: use with caution in elderly who may be more susceptible to dicyclomine hydrochloride’s adverse events (5.10)

6 ADVERSE REACTIONS

The most serious adverse reactions include cardiovascular and central nervous system symptoms. The most common adverse reactions (> 5% of patients) are dizziness, dry mouth, vision blurred, nausea, somnolence, asthenia and nervousness (6)

To report SUSPECTED ADVERSE REACTIONS, Slate Run Pharmaceuticals, LLC at 1-888-341-9214 or FDA at 1-800-FDA-1088 or www.fda.gov/medwatch.

7 DRUG INTERACTIONS

- Antiglaucoma agents: anticholinergics antagonize antiglaucoma agents and may increase intraocular pressure (7)
- Anticholinergic agents: may affect the gastrointestinal absorption of various drugs; may also increase certain actions or side effects of other anticholinergic drugs (7)
- Antacids: interfere with the absorption of anticholinergic agents (7)

8 USE IN SPECIFIC POPULATIONS

- Pregnancy: use only if clearly needed (8.1)
- Pediatric Use: Safety and effectiveness not established (8.4)
- Hepatic and renal impairment: caution must be taken with patients with significantly impaired hepatic and renal function (8.6)

FULL PRESCRIBING INFORMATION

1 INDICATIONS AND USAGE

Dicyclomine hydrochloride is indicated for the treatment of patients with functional bowel/irritable bowel syndrome.

2 DOSAGE AND ADMINISTRATION

Dosage must be adjusted to individual patient needs.

2.1 Intramuscular Dosage and Administration in Adults

Dicyclomine hydrochloride intramuscular injection must be administered via intramuscular route only. Do not administer by any other route.

The recommended intramuscular dose is 10 mg to 20 mg four times a day [see Clinical Pharmacology (12)].

The intramuscular injection is to be used only for 1 or 2 days when the patient cannot take oral medication.

Intramuscular injection is about twice as bioavailable as oral dosage forms.

2.2 Preparation for Intramuscular Administration

Parenteral drug products should be inspected visually for particulate matter and discoloration prior to administration, whenever solution and container permit.

Aspirate the syringe before injecting to avoid intravascular injection, since thrombosis may occur if the drug is inadvertently injected intravascularly.

3 DOSAGE FORMS AND STRENGTHS

- Dicyclomine Hydrochloride Injection, USP, 20 mg/2 mL (10 mg/mL)

4 CONTRAINDICATIONS

Dicyclomine hydrochloride is contraindicated in infants less than 6 months of age [see Use in Specific Populations (8.4)] , nursing mothers [see Use in Specific Populations (8.3)] , and in patients with:

- unstable cardiovascular status in acute hemorrhage
- myasthenia gravis [see Warnings and Precautions (5.4)]
- glaucoma [see Adverse Reactions (6.3) and Drug Interactions (7.1)]
- obstructive uropathy [see Warnings and Precautions (5.8)]
- obstructive disease of the gastrointestinal tract [see Warnings and Precautions (5.5)]
- severe ulcerative colitis [see Warnings and Precautions (5.7)]
- reflux esophagitis

5 WARNINGS AND PRECAUTIONS

5.1 Inadvertent Intravenous Administration

Dicyclomine hydrochloride solution is for intramuscular administration only. Do not administer by any other route. Inadvertent intravenous administration may result in thrombosis, thrombophlebitis, and injection site reactions such as pain, edema, skin color change, and reflex sympathetic dystrophy syndrome [see Adverse Reactions (6.2)] .

5.2 Cardiovascular Conditions

Dicyclomine hydrochloride needs to be used with caution in conditions characterized by tachyarrhythmia such as thyrotoxicosis, congestive heart failure and in cardiac surgery, where they may further accelerate the heart rate. Investigate any tachycardia before administration of dicyclomine hydrochloride. Care is required in patients with coronary heart disease, as ischemia and infarction may be worsened, and in patients with hypertension [see Adverse Reactions (6.3)] .

5.3 Peripheral and Central Nervous System

The peripheral effects of dicyclomine hydrochloride are a consequence of their inhibitory effect on muscarinic receptors of the autonomic nervous system. They include dryness of the mouth with difficulty in swallowing and talking, thirst, reduced bronchial secretions, dilatation of the pupils (mydriasis) with loss of accommodation (cycloplegia) and photophobia, flushing and dryness of the skin, transient bradycardia followed by tachycardia, with palpitations and arrhythmias, and difficulty in micturition, as well as reduction in the tone and motility of the gastrointestinal tract leading to constipation [see Adverse Reactions (6)] .

In the presence of high environmental temperature heat prostration can occur with drug use (fever and heat stroke due to decreased sweating). It should also be used cautiously in patients with fever. If symptoms occur, the drug should be discontinued and supportive measures instituted. Because of the inhibitory effect on muscarinic receptors within the autonomic nervous system, caution should be taken in patients with autonomic neuropathy.

Central nervous system (CNS) signs and symptoms include confusional state, disorientation, amnesia, hallucinations, dysarthria, ataxia, coma, euphoria, fatigue, insomnia, agitation and mannerisms, and inappropriate affect.

Psychosis and delirium have been reported in sensitive individuals (such as elderly patients and/or in patients with mental illness) given anticholinergic drugs. These CNS signs and symptoms usually resolve within 12 to 24 hours after discontinuation of the drug.

Dicyclomine hydrochloride may produce drowsiness, dizziness or blurred vision. The patient should be warned not to engage in activities requiring mental alertness, such as operating a motor vehicle or other machinery or performing hazardous work while taking dicyclomine hydrochloride.

5.4 Myasthenia Gravis

With overdosage, a curare-like action may occur (i.e., neuromuscular blockade leading to muscular weakness and possible paralysis). It should not be given to patients with myasthenia gravis except to reduce adverse muscarinic effects of an anticholinesterase [see Contraindications (4)].

5.5 Intestinal Obstruction

Diarrhea may be an early symptom of incomplete intestinal obstruction, especially in patients with ileostomy or colostomy. In this instance, treatment with this drug would be inappropriate and possibly harmful [see Contraindications (4)].

Rarely development of Ogilvie’s syndrome (colonic pseudo-obstruction) has been reported. Ogilvie’s syndrome is a clinical disorder with signs, symptoms, and radiographic appearance of an acute large bowel obstruction but with no evidence of distal colonic obstruction

5.6 Toxic Dilatation of Intestinemegacolon

Toxic dilatation of intestine and intestinal perforation is possible when anticholinergic agents are administered in patients with Salmonella dysentery.

5.7 Ulcerative Colitis

Caution should be taken in patients with ulcerative colitis. Large doses may suppress intestinal motility to the point of producing a paralytic ileus and the use of this drug may precipitate or aggravate the serious complication of toxic megacolon [see Adverse Reactions (6.3)] . Dicyclomine hydrochloride is contraindicated in patients with severe ulcerative colitis [see Contraindications (4)].

5.8 Prostatic Hypertrophy

Dicyclomine hydrochloride should be used with caution in patients with known or suspected prostatic enlargement, in whom prostatic enlargement may lead to urinary retention [see Adverse Reactions (6.3)] .

5.9 Hepatic and Renal Disease

Dicyclomine hydrochloride should be used with caution in patients with known hepatic and renal impairment.

5.10 Geriatric Population

Dicyclomine hydrochloride should be used with caution in elderly who may be more susceptible to its adverse effects.

6 ADVERSE REACTIONS

The pattern of adverse effects seen with dicyclomine is mostly related to its pharmacological actions at muscarinic receptors [see Clinical Pharmacology (12)] . They are a consequence of the inhibitory effect on muscarinic receptors within the autonomic nervous system. These effects are dose-related and are usually reversible when treatment is discontinued.

The most serious adverse reactions reported with dicyclomine hydrochloride include cardiovascular and central nervous system symptoms [see Warnings and Precautions (5.2, 5.3)].

6.1 Clinical Trials Experience

Because clinical trials are conducted under widely varying conditions, adverse reaction rates observed in the clinical trials of a drug cannot be directly compared to rates in the clinical trials of another drug and may not reflect the rates observed in practice.

The data described below reflect exposure in controlled clinical trials involving over 100 patients treated for functional bowel/irritable bowel syndrome with dicyclomine hydrochloride at initial doses of 160 mg daily (40 mg four times a day).

In these trials most of the side effects were typically anticholinergic in nature and were reported by 61% of the patients. Table 1presents adverse reactions (MedDRA 13.0 preferred terms) by decreasing order of frequency in a side-by-side comparison with placebo.

Table 1: Adverse reactions experienced in controlled clinical trials with decreasing order of frequency

MedDRA Preferred Term | Dicyclomine Hydrochloride; (40 mg four times a day) % | Placebo %
Dry Mouth | 33 | 5
Dizziness | 40 | 5
Vision Blurred | 27 | 2
Nausea | 14 | 6
Somnolence | 9 | 1
Asthenia | 7 | 1
Nervousness | 6 | 2

Nine percent (9%) of patients were discontinued from dicyclomine hydrochloride because of one or more of these side effects (compared with 2% in the placebo group). In 41% of the patients with side effects, side effects disappeared or were tolerated at the 160 mg daily dose without reduction. A dose reduction from 160 mg daily to an average daily dose of 90 mg was required in 46% of the patients with side effects who then continued to experience a favorable clinical response; their side effects either disappeared or were tolerated.

6.2 Postmarketing Experience

The following adverse reactions, presented by system organ class in alphabetical order, have been identified during post approval use of dicyclomine hydrochloride. Because these reactions are reported voluntarily from a population of uncertain size, it is not always possible to reliably estimate their frequency or establish a causal relationship to drug exposure.

- Cardiac disorders:palpitations, tachyarrhythmias
- Eye disorders:cycloplegia, mydriasis, vision blurred
- Gastrointestinal disorders:abdominal distension, abdominal pain, constipation, dry mouth, dyspepsia, nausea, vomiting
- General disorders and administration site conditions:fatigue, malaise
- Immune system disorders:drug hypersensitivity including face edema, angioedema, anaphylactic shock
- Nervous system disorders:dizziness, headache, somnolence, syncope
- Psychiatric disorders:As with the other anti-cholinergic drugs, cases of delirium or symptoms of delirium such as amnesia (or transient global amnesia), agitation, confusional state, delusion, disorientation, hallucination (including visual hallucination) as well as mania, mood altered and pseudodementia, have been reported with the use of dicyclomine. Nervousness and insomnia have also been reported.
- Reproductive system and breast disorders:suppressed lactation
- Respiratory, thoracic and mediastinal disorders:dyspnea, nasal congestion
- Skin and subcutaneous tissue disorder:dermatitis allergic, erythema, rash

Cases of thrombosis, thrombophlebitis and injection site reactions such as local pain, edema, skin color change and even reflex sympathetic dystrophy syndrome have been reported following inadvertent IV injection of dicyclomine hydrochloride.

6.3 Adverse Reactions Reported with Similar Drugs with Anticholinergic/Antispasmodic Action

Gastrointestinal: anorexia

Central Nervous System: tingling, numbness, dyskinesia, speech disturbance, insomnia

Peripheral Nervous System: with overdosage, a curare-like action may occur (i.e., neuromuscular blockade leading to muscular weakness and possible paralysis)

Ophthalmologic: diplopia, increased ocular tension

Dermatologic/Allergic: urticaria, itching, and other dermal manifestations

Genitourinary: urinary hesitancy, urinary retention in patients with prostatic hypertrophy

Cardiovascular: hypertension

Respiratory: apnea

Other: decreased sweating, sneezing, throat congestion, impotence. With the injectable form, there may be temporary sensation of light-headedness. Some local irritation and focal coagulation necrosis may occur following the intramuscular injection of dicyclomine hydrochloride.

7 DRUG INTERACTIONS

7.1 Antiglaucoma Agents

Anticholinergics antagonize the effects of antiglaucoma agents. Anticholinergic drugs in the presence of increased intraocular pressure may be hazardous when taken concurrently with agents such as corticosteroids. Use of dicyclomine hydrochloride in patients with glaucoma is not recommended [see Contraindications (4)].

7.2 Other Drugs with Anticholinergic Activity

The following agents may increase certain actions or side effects of anticholinergic drugs including dicyclomine hydrochloride: amantadine, antiarrhythmic agents of Class I (e.g., quinidine), antihistamines, antipsychotic agents (e.g., phenothiazines), benzodiazepines, MAO inhibitors, narcotic analgesics (e.g., meperidine), nitrates and nitrites, sympathomimetic agents, tricyclic antidepressants, and other drugs having anticholinergic activity.

7.3 Other Gastrointestinal Motility Drugs

Interaction with other gastrointestinal motility drugs may antagonize the effects of drugs that alter gastrointestinal motility, such as metoclopramide.

7.4 Effect of Antacids

Because antacids may interfere with the absorption of anticholinergic agents including dicyclomine hydrochloride, simultaneous use of these drugs should be avoided.

7.5 Effect on Absorption of Other Drugs

Anticholinergic agents may affect gastrointestinal absorption of various drugs by affecting on gastrointestinal motility, such as slowly dissolving dosage forms of digoxin; increased serum digoxin concentration may result.

7.6 Effect on Gastric Acid Secretion

The inhibiting effects of anticholinergic drugs on gastric hydrochloric acid secretion are antagonized by agents used to treat achlorhydria and those used to test gastric secretion.

8 USE IN SPECIFIC POPULATIONS

8.1 Pregnancy

Adequate and well-controlled studies have not been conducted with dicyclomine hydrochloride in pregnant women at the recommended doses of 80 to 160 mg/day. However, epidemiologic studies did not show an increased risk of structural malformations among babies born to women who took products containing dicyclomine hydrochloride at doses up to 40 mg/day during the first trimester of pregnancy. Reproduction studies have been performed in rats and rabbits at doses up to 33 times the maximum recommended human dose based on 160 mg/day (3 mg/kg) and have revealed no evidence of harm to the fetus due to dicyclomine. Because animal reproduction studies are not always predictive of human response, this drug should be used during pregnancy only if clearly needed.

8.3 Nursing Mothers

Dicyclomine hydrochloride is contraindicated in women who are breastfeeding. Dicyclomine hydrochloride is excreted in human milk. Because of the potential for serious adverse reactions in breast-fed infants from dicyclomine hydrochloride, a decision should be made whether to discontinue nursing or to discontinue the drug, taking into account the importance of the drug to the mother [see Use in Specific Populations (8.4)] .

8.4 Pediatric Use

Safety and effectiveness in pediatric patients have not been established.

Dicyclomine hydrochloride is contraindicated in infants less than 6 months of age [see Contraindications (4)] . There are published cases reporting that the administration of dicyclomine hydrochloride to infants has been followed by serious respiratory symptoms (dyspnea, shortness of breath, breathlessness, respiratory collapse, apnea and asphyxia), seizures, syncope, pulse rate fluctuations, muscular hypotonia, and coma, and death, however; no causal relationship has been established.

8.5 Geriatric Use

Clinical studies of dicyclomine hydrochloride did not include sufficient numbers of subjects aged 65 and over to determine whether they respond differently from younger subjects. Other reported clinical experience has not identified differences in responses between the elderly and younger patients. In general, dose selection for an elderly patient should be cautious, usually starting at the low end of the dosing range in adults, reflecting the greater frequency of decreased hepatic, renal, or cardiac function, and of concomitant disease or other drug therapy.

Because elderly patients are more likely to have decreased renal function, care should be taken in dose selection, and it may be useful to monitor renal function.

8.6 Renal Impairment

Effects of renal impairment on PK, safety and efficacy of dicyclomine hydrochloride have not been studied. Dicyclomine hydrochloride drug is known to be substantially excreted by the kidney, and the risk of toxic reactions to this drug may be greater in patients with impaired renal function. Dicyclomine hydrochloride should be administered with caution in patients with renal impairment.

8.7 Hepatic Impairment

Effects of renal impairment on PK, safety and efficacy of dicyclomine hydrochloride have not been studied. Dicyclomine hydrochloride should be administered with caution in patients with hepatic impairment.

10 OVERDOSAGE

In case of an overdose, patients should contact a physician, poison control center (1-800-222-1222), or emergency room.

The signs and symptoms of overdosage include: headache; nausea; vomiting; blurred vision; dilated pupils; hot, dry skin; dizziness; dryness of the mouth; difficulty in swallowing; and CNS stimulation including convulsion. A curare-like action may occur (i.e., neuromuscular blockade leading to muscular weakness and possible paralysis).

One reported event included a 37-year-old who reported numbness on the left side, cold fingertips, blurred vision, abdominal and flank pain, decreased appetite, dry mouth, and nervousness following ingestion of 320 mg daily (four 20 mg tablets four times daily). These events resolved after discontinuing the dicyclomine.

The acute oral LD50 of the drug is 625 mg/kg in mice.

The amount of drug in a single dose that is ordinarily associated with symptoms of overdosage or that is likely to be life-threatening, has not been defined. The maximum human oral dose recorded was 600 mg by mouth in a 10-month-old child and approximately 1500 mg in an adult, each of whom survived. In three of the infants who died following administration of dicyclomine hydrochloride [see Warnings and Precautions (5.1)] , the blood concentrations of drug were 200, 220, and 505 ng/mL.

It is not known if dicyclomine hydrochloride is dialyzable.

Treatment should consist of gastric lavage, emetics, and activated charcoal. Sedatives (e.g., short-acting barbiturates, benzodiazepines) may be used for management of overt signs of excitement. If indicated, an appropriate parenteral cholinergic agent may be used as an antidote.

11 DESCRIPTION

Dicyclomine hydrochloride is an antispasmodic and anticholinergic (antimuscarinic) agent available in the following dosage form:

- Dicyclomine Hydrochloride Injection, USP is a sterile, pyrogen-free, aqueous solution for intramuscular injection (NOT FOR INTRAVENOUS USE) supplied as a vial containing 20 mg/2 mL (10 mg/mL). Each mL contains 10 mg dicyclomine hydrochloride USP in sterile water for injection, made isotonic with sodium chloride.

Dicyclomine hydrochloride is [bicyclohexyl]-1- carboxylic acid, 2-(diethylamino) ethyl ester, hydrochloride, with a molecular formula of C19H35NO2•HCl and the following structural formula:

Molecular weight: 345.95

Dicyclomine Hhydrochloride occurs as a fine, white, crystalline, practically odorless powder with a bitter taste. It is soluble in water, freely soluble in alcohol and chloroform, and very slightly soluble in ether.

12 CLINICAL PHARMACOLOGY

12.1 Mechanism of Action

Dicyclomine relieves smooth muscle spasm of the gastrointestinal tract. Animal studies indicate that this action is achieved via a dual mechanism:

- a specific anticholinergic effect (antimuscarinic) at the acetylcholine-receptor sites with approximately 1/8 the milligram potency of atropine (in vitro, guinea pig ileum); and
- a direct effect upon smooth muscle (musculotropic) as evidenced by dicyclomine’s antagonism of bradykinin- and histamine-induced spasms of the isolated guinea pig ileum.

Atropine did not affect responses to these two agonists. In vivo studies in cats and dogs showed dicyclomine to be equally potent against acetylcholine (ACh)- or barium chloride (BaCl2)-induced intestinal spasm while atropine was at least 200 times more potent against effects of ACh than BaCl2. Tests for mydriatic effects in mice showed that dicyclomine was approximately 1/500 as potent as atropine; antisialagogue tests in rabbits showed dicyclomine to be 1/300 as potent as atropine.

12.2 Pharmacodynamics

Dicyclomine hydrochloride can inhibit the secretion of saliva and sweat, decrease gastrointestinal secretions and motility, cause drowsiness, dilate the pupils, increase heart rate, and depress motor function.

12.3 Pharmacokinetics

Absorption and Distribution

In man, dicyclomine is rapidly absorbed after oral administration, reaching peak values within 60-90 minutes. Mean volume of distribution for a 20 mg oral dose is approximately 3.65 L/kg suggesting extensive distribution in tissues.

Elimination

The metabolism of dicyclomine was not studied. The principal route of excretion is via the urine (79.5% of the dose). Excretion also occurs in the feces, but to a lesser extent (8.4%). Mean half-life of plasma elimination in one study was determined to be approximately 1.8 hours when plasma concentrations were measured for 9 hours after a single dose. In subsequent studies, plasma concentrations were followed for up to 24 hours after a single dose, showing a secondary phase of elimination with a somewhat longer half-life.

13 NONCLINICAL TOXICOLOGY

13.1 Carcinogenesis, Mutagenesis, Impairment of Fertility

Long-term animal studies have not been conducted to evaluate the carcinogenic potential of dicyclomine. In studies in rats at doses of up to 100 mg/kg/day, dicyclomine produced no deleterious effects on breeding, conception, or parturition.

14 CLINICAL STUDIES

In controlled clinical trials involving over 100 patients who received drug, 82% of patients treated for functional bowel/irritable bowel syndrome with dicyclomine hydrochloride at initial doses of 160 mg daily (40 mg four times daily) demonstrated a favorable clinical response compared with 55% treated with placebo (p<0.05).

16 HOW SUPPLIED/STORAGE AND HANDLING

Dicyclomine Hydrochloride Injection, USP is available as follows:

Unit of Sale | Units per Carton | Strength | Each
70436-147-81 | 5 vials per carton | 20 mg/2 mL; (10 mg/mL) | 70436-147-80; 2 mL single dose vial

Store at room temperature, preferably below 86°F (30°C). Protect from freezing.

17 PATIENT COUNSELING INFORMATION

17.1 Inadvertent Intravenous Administration

Dicyclomine hydrochloride injection is for intramuscular administration only. Do not administer by any other route. Inadvertent administration may result in thrombosis or thrombophlebitis, and injection site such as pain, edema, skin color change and even reflex sympathetic dystrophy syndrome [see Adverse Reactions (6.2)] .

17.2 Use in Infants

Inform parents and caregivers not to administer dicyclomine hydrochloride in infants less than 6 months of age [see Use in Specific Populations (8.4)] .

17.3 Use in Nursing Mothers

Advise lactating women that dicyclomine hydrochloride should not be used while breastfeeding their infants [see Use in Specific Populations (8.3, 8.4)] .

17.4 Peripheral and Central Nervous System

In the presence of a high environmental temperature, heat prostration can occur with dicyclomine hydrochloride use (fever and heat stroke due to decreased sweating). If symptoms occur, the drug should be discontinued and a physician contacted. Dicyclomine hydrochloride may produce drowsiness or blurred vision. The patient should be warned not to engage in activities requiring mental alertness, such as operating a motor vehicle or other machinery or to perform hazardous work while taking dicyclomine hydrochloride [see Warnings and Precautions (5.3)].

Rx only

Manufactured by:
Hainan Poly Pharm. Co., Ltd., Guilinyang Economic Development Zone, Haikou, Hainan, China 57112

Distributed by:

Slate Run Pharmaceuticals, LLC, Columbus, Ohio 43215

10000180/02

Revised 01/2026

PRINCIPAL DISPLAY PANEL

NDC 70436-147-80
Dicyclomine Hydrochloride Injection, USP
20 mg/2 mL (10 mg/mL)
For Intramuscular Use Only

PRINCIPAL DISPLAY PANEL

NDC 70436-147-81

Dicyclomine Hydrochloride Injection, USP
20 mg/2 mL (10 mg/mL)
For Intramuscular Use Only